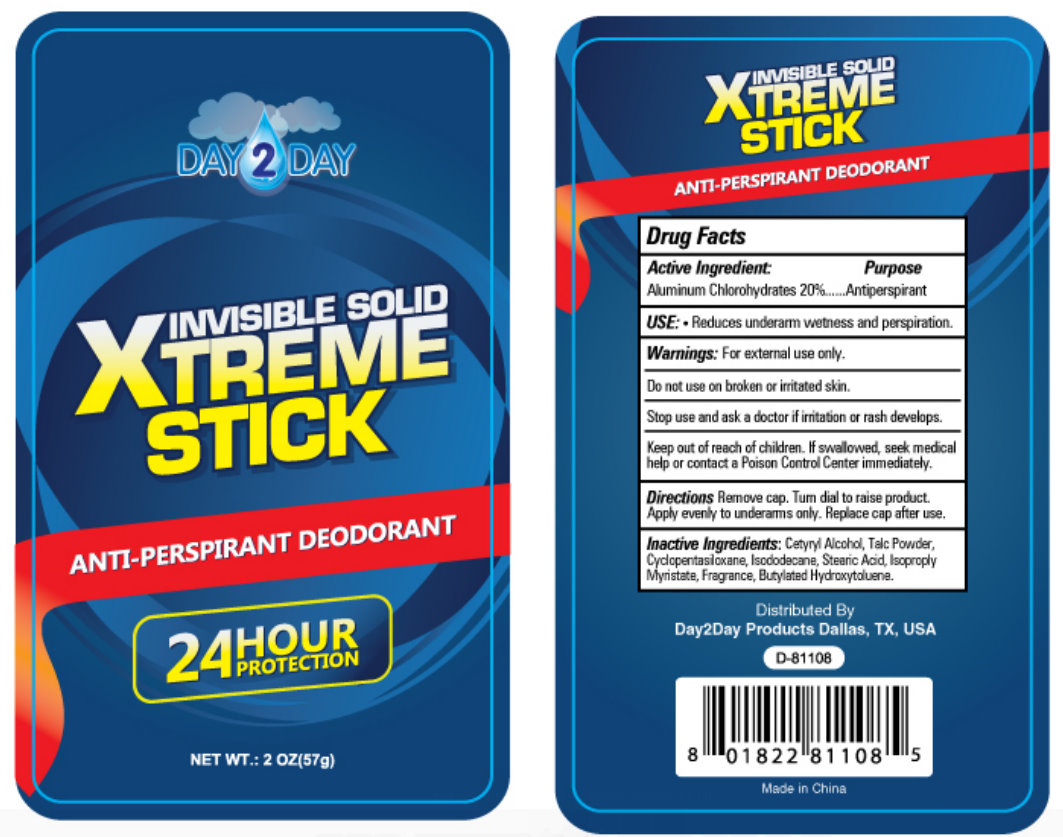 DRUG LABEL: Invisible Solid Xtreme Anti-Perspirant Deodorant
NDC: 76088-100 | Form: STICK
Manufacturer: King Import Warehouse
Category: otc | Type: HUMAN OTC DRUG LABEL
Date: 20110330

ACTIVE INGREDIENTS: ALUMINUM CHLOROHYDRATE 20 g/100 g
INACTIVE INGREDIENTS: TALC; CYCLOMETHICONE 5; ISODODECANE; STEARIC ACID; ISOPROPYL MYRISTATE; BUTYLATED HYDROXYTOLUENE; CETYL ALCOHOL

DAY2DAY INVISIBLE SOLID XTREME STICK ANTI-PERSPIRANT DEODORANT

Active Ingredient:

Aluminum Chlorohydrate 20%

PURPOSE

Antiperspirant

INDICATIONS AND USAGE

Use: Reduces underarm wetness and perspiration.

Warnings: for external use only.

Do not use on broken or irritated skin.

Stop use and ask a doctor if irritation or rash develops

Keep out of reach of children. If swallowed, seek medical help or contact a Poison Control Center immediately

DOSAGE AND ADMINISTRATION

Directions: Remove cap. Turn dial to raise product. Apply evenly to underarms only. Replace cap after use.

INACTIVE INGREDIENT

Inactive Ingredients: Cetyryl Alcohol, Talc Powder, Cyclopentasiloxane, Isododecane, Stearic Acid, Isopropyl Myristate, Fragrance, Butylated Hydroxytoluene

PACKAGE LABEL

DAY2DAY
INVISIBLE SOLID
XTREME STICK
ANTI-PERSPIRANT DEODORANT
24 HOUR PROTECTION
NET WT.: 2OZ(58g)